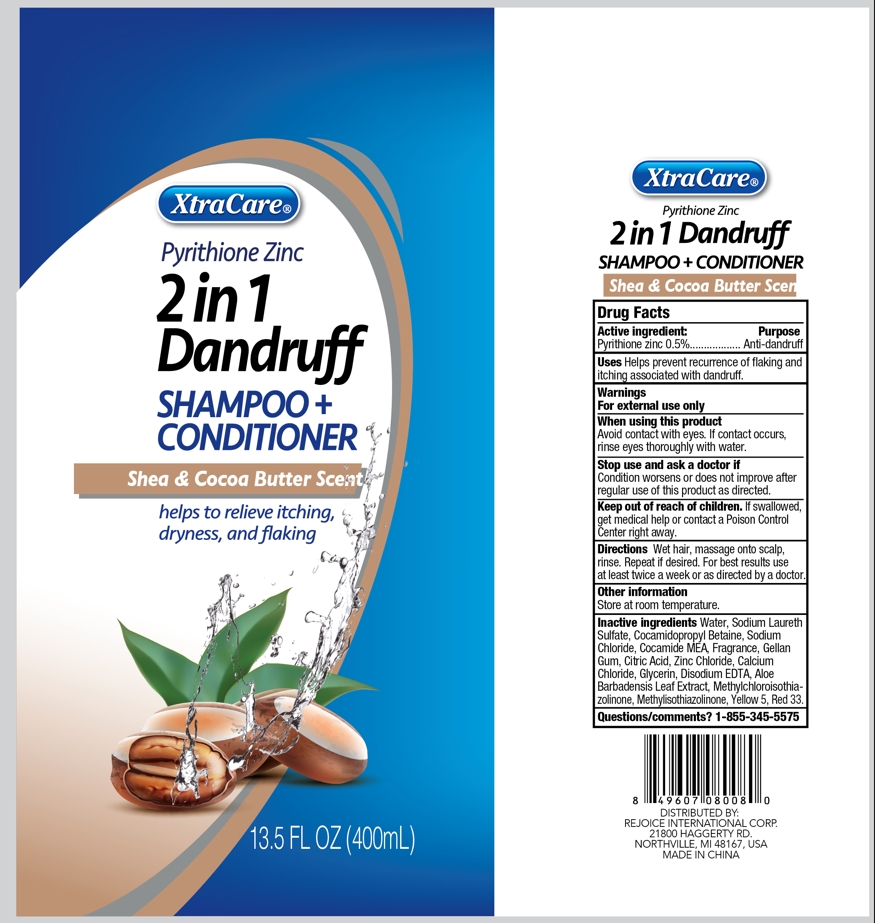 DRUG LABEL: 13.5oz 2 In 1 Dandruff Hair Cleanse and Conditioner - Shea and Cocoa Butter
NDC: 57337-179 | Form: SHAMPOO
Manufacturer: Rejoice International Corp.
Category: otc | Type: HUMAN OTC DRUG LABEL
Date: 20250317

ACTIVE INGREDIENTS: PYRITHIONE ZINC 0.5 g/100 mL
INACTIVE INGREDIENTS: METHYLISOTHIAZOLINONE; CITRIC ACID; RED 33; GELLAN GUM; SODIUM LAURETH SULFATE; YELLOW 5; COCAMIDE MEA; ZINC CHLORIDE; CALCIUM CHLORIDE; METHYLCHLOROISOTHIAZOLINONE; WATER; SODIUM CHLORIDE; COCAMIDOPROPYL BETAINE; EDETATE DISODIUM; ALOE VERA LEAF; GLYCERIN

13.5oz 2 In 1 Dandruff Hair Cleanse and Conditioner - Shea and Cocoa Butter

Active ingredient

Pyrithione Zinc 0.5%

Purpose

Anti-dandruff

Use

Helps prevent recurrence of flaking and itching associsted with dandruff.

Warnings

For external use only

When using this product

Avoid contact with eyes. If contact occurs, rinse eyes thoroughly with water.

Stop use and ask a doctor if

Condition worsens or does not improve after regular use of this products as directed.

Keep out of reach of children

If swallowed, get medical help or contact a Poison Control Center right away.

Directions

Wet hair, massage onto scalp, rinse. Repeat if desired. For best resultd use at least twice a week or as directed by a doctor.

Other information

Store at room temperature.

Inactive ingredients

Water

Sodium Laureth Sulfate

Cocamidopropyl Betaine

Sodium Chloride

Cocamide MEA

Fragrance

Gellan Gum

Citric Acid

Zinc Chloride

Calcium Chloride

Glycerin

Disodium EDTA

Aloe Barbadensis Leaf Extract

Methylchloroisothiazolinone

Methylisothiazolinone

Yellow 5

Red 33